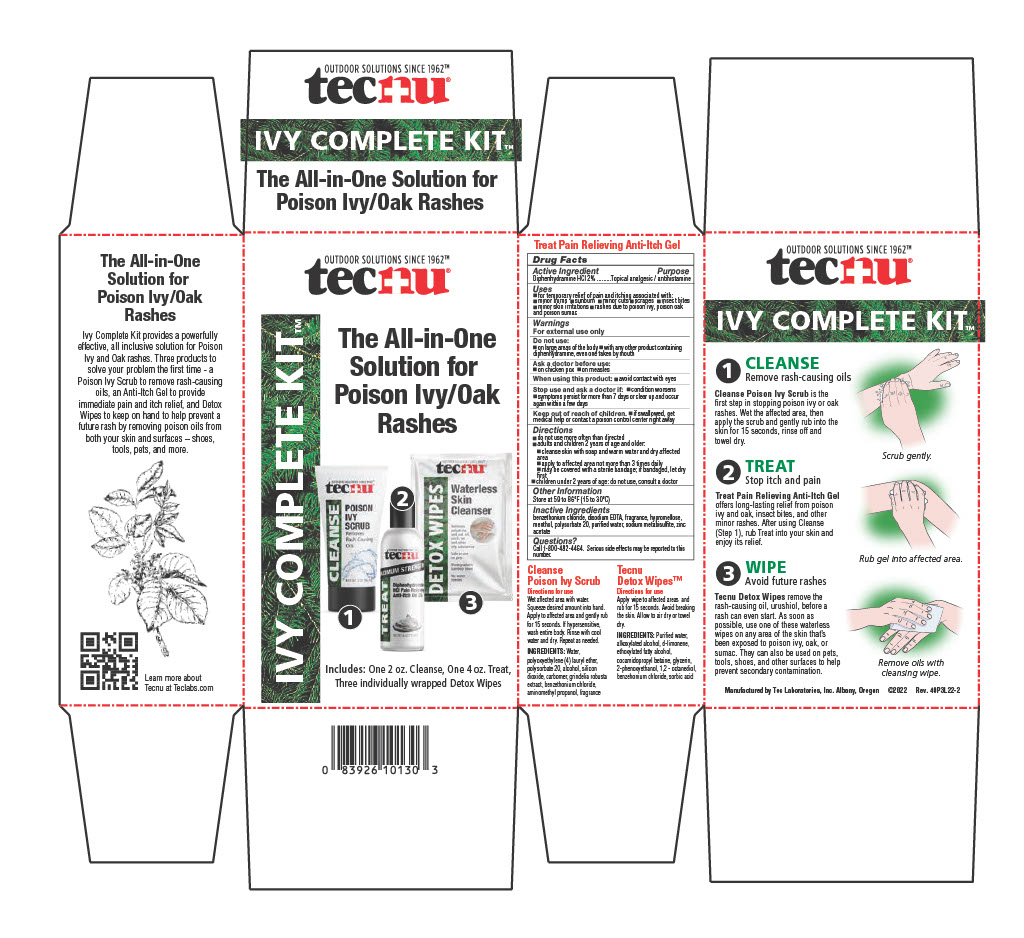 DRUG LABEL: Tecnu Ivy Complete Kit
NDC: 51879-400 | Form: KIT | Route: TOPICAL
Manufacturer: Tec Laboratories Inc.
Category: otc | Type: HUMAN OTC DRUG LABEL
Date: 20241218

ACTIVE INGREDIENTS: DIPHENHYDRAMINE HYDROCHLORIDE 20 mg/1 g
INACTIVE INGREDIENTS: MENTHOL, UNSPECIFIED FORM; POLYSORBATE 20; EDETATE DISODIUM; BENZETHONIUM CHLORIDE; WATER; ZINC ACETATE; HYPROMELLOSE 2208 (100 MPA.S)

ACTIVE INGREDIENT

Diphenhydramine HCL 2%

Purpose Topical analgesic/antihistamine

INDICATIONS AND USAGE

for the temporary relief of pain and itching associated with:

•minor burns•sunburn•minor cuts•scrapes•insect bites

•minor skin irritaitons

•rashes due to poison ivy, poison oak and poison sumac

Do not use:

- on large areas of the body
- with any other product containing diphenhydramine, even on taken by mouth

Ask a doctor before use:

- on chicken pox
- on measles

Keep out of reach of children.

- if swallowed, get medical help or contact a poison control center right away

When using this product:

- avoid contact with eyes

Stop use and ask a doctor if:

- condition worsens
- symptoms persist for more than 7 days or clear up and occur again within a few days

Directions

- do not use more than directed
- adults and children 2 years of age and older:
  - cleanse skin with soap and warm water and dry affected area
  - apply to affected area not more than 3 times daily
  - may be covered with a bandage; if bandage let dry first
  - children under 2 years of age: do not use, consult a doctor

Other information

Store at 59 to 86°F (15 to 30°C)

INACTIVE INGREDIENT

benzethonium chloride, disodium EDTA, fragrance, hypromellose, menthol, polysorbate 20, purified water, sodium metabisulfite, zinc acetate

Questions?

Call 1-800-482-4464

Serious side effects may be reported to this number